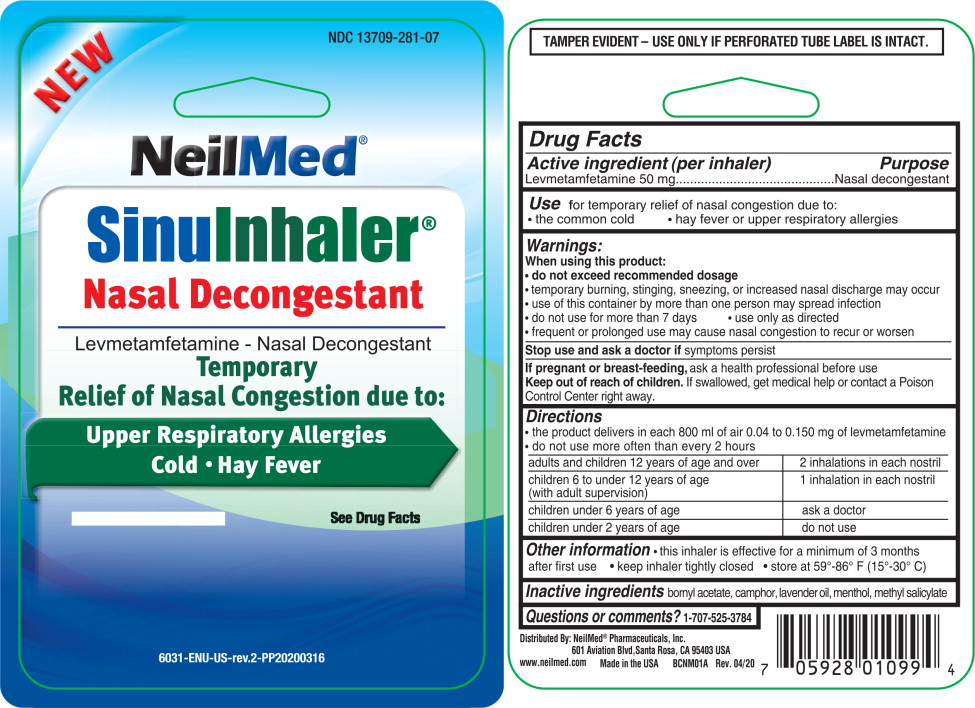 DRUG LABEL: Sinu Inhaler
NDC: 13709-281 | Form: INHALANT
Manufacturer: NeilMed Pharmaceuticals, Inc.
Category: otc | Type: HUMAN OTC DRUG LABEL
Date: 20181218

ACTIVE INGREDIENTS: Levmetamfetamine 50 mg/1 1
INACTIVE INGREDIENTS: Bornyl acetate; Camphor (Synthetic); Lavender oil; Menthol; Methyl Salicylate

Drug Facts

Active ingredient (per inhaler)

Levmetamfetamine 50 mg

Purpose

Nasal decongestant

Use for temporary relief of nasal congestion due to:

- the common cold
- hay fever or upper respiratory allergies

When using this product

- do not exceed recommended dosage
- temporary burning, stinging, sneezing, or increased nasal discharge may occur
- use of this container by more than one person may spread infection
- do not use for more than 7 days
- Use only as directed
- frequent or prolonged use may cause nasal congestion to recur or worsen

Stop use and ask a doctor if

symptoms persist

If pregnant or breast-feeding,

ask a health professional before use.

Keep out of reach of children.

If swallowed, get medical help or contact a Poison Control Center right away.

Directions

- the product delivers in each 800 ml of air 0.04 to 0.150 mg of levmetamfetamine
- do not use more often than every 2 hours

adults and children 12 years of age and over | 2 inhalations in each nostril
children 6 to under 12 years of age; (with adult supervision) | 1 inhalation in each nostril
children under 6 years of age | ask a doctor
children under 2 years of age | do not use

Other Information

- this inhaler is effective for a minimum of 3 months after first use
- keep inhaler tightly closed
- store at 59o-86oF (15o- 30oC)

Inactive Ingredients:

bornyl acetate, camphor, lavender oil, menthol, methyl salicylate

Questions or comments? 1-707-525-3784

TAMPER EVIDENT - USE ONLY IF PERFORATED TUBE LABEL IS INTACT

DISTRIBUTED BY NeilMed® Pharmaceuticals, Inc.

601 Aviation Blvd., Santa Rosa, CA 95403 USA

www.NeilMed.com Made in the USA BCNM01 Rev. 04/14

PRINCIPAL DISPLAY PANEL - Sinu Inhaler

NEW

NDC 13709-281-07

NeilMed®

Sinu Inhaler™

Nasal Decongestant

_______________________

Levmetamfetamine - Nasal Decongestant

Temporary

Relief of Nasal Congestion due to:

Upper Respiratory Allergies

Cold • Hay Fever

Net Wt 0.007 OZ (198 mg) See Drug Facts

6031-ENU-US-rev1-PP20140409zm